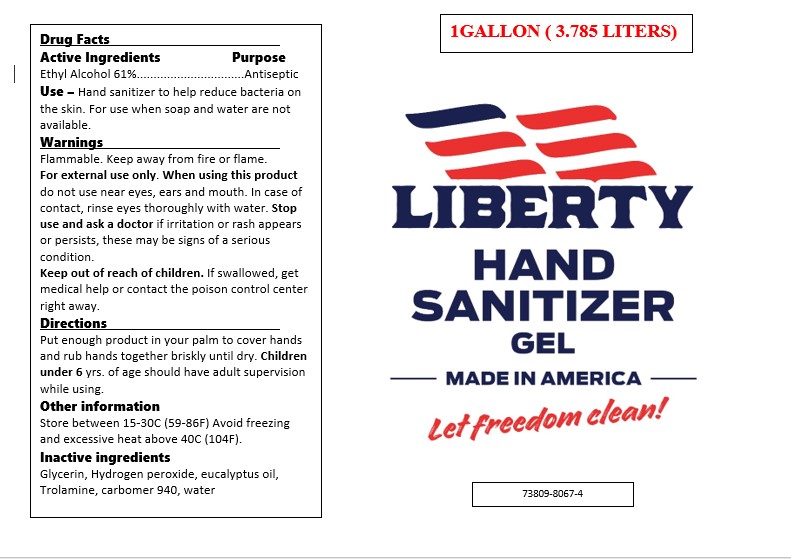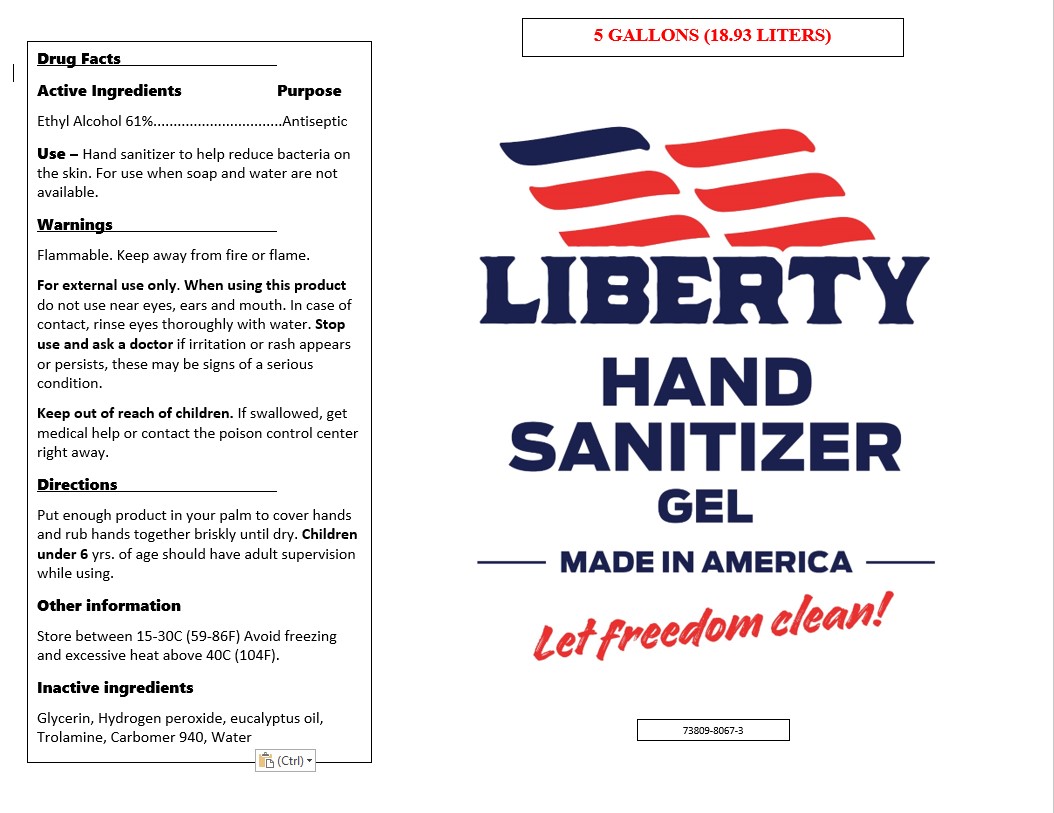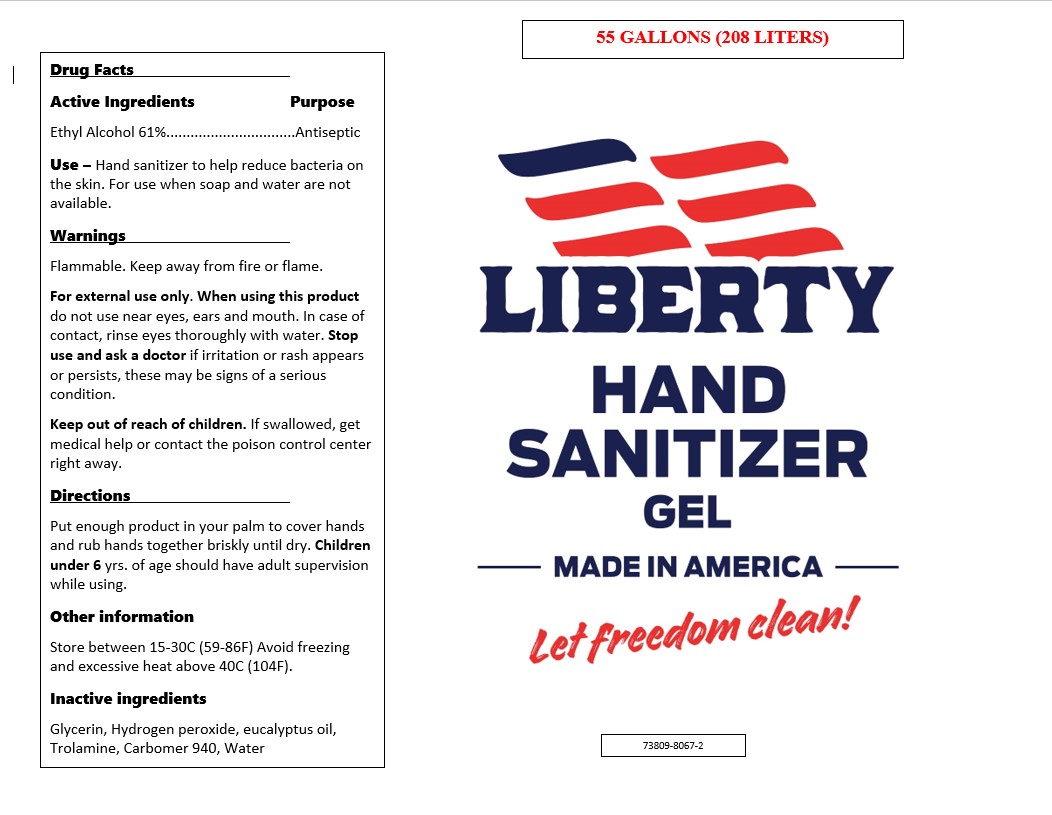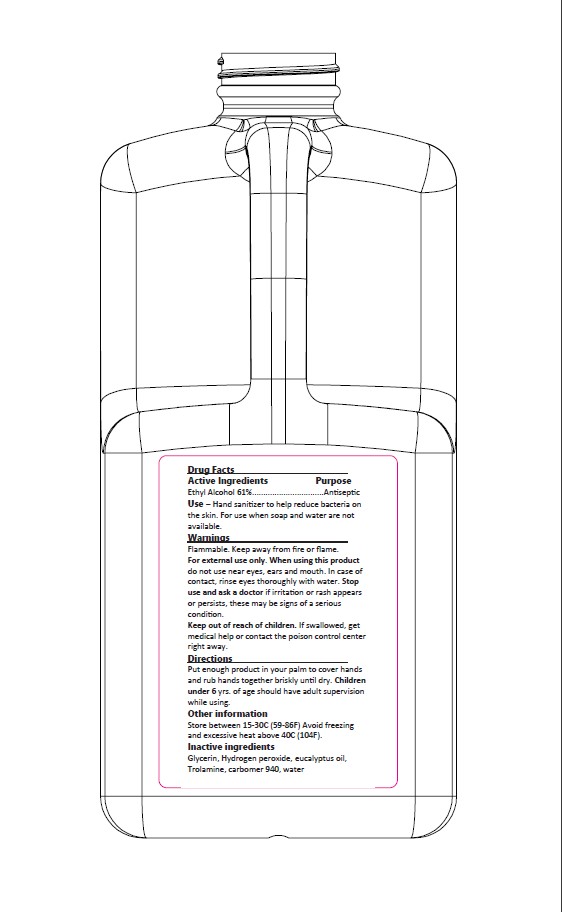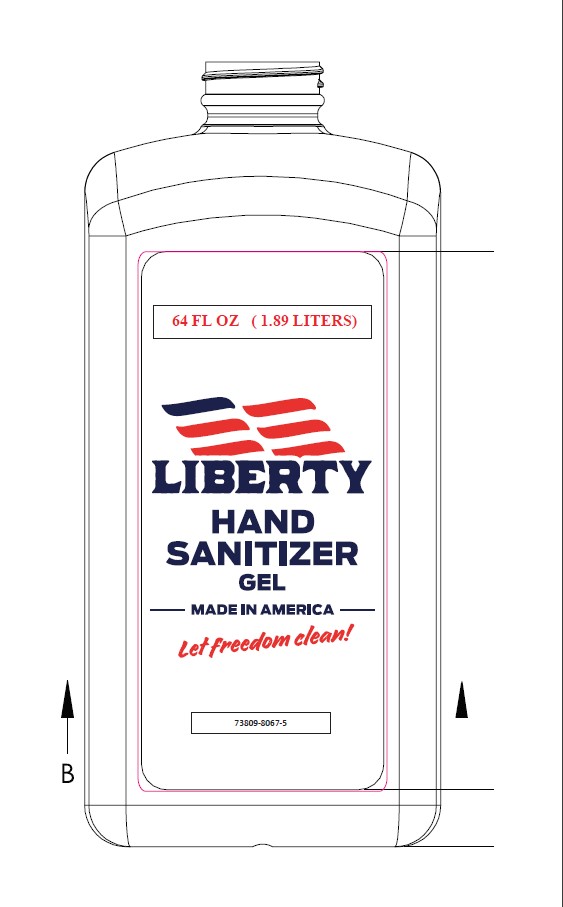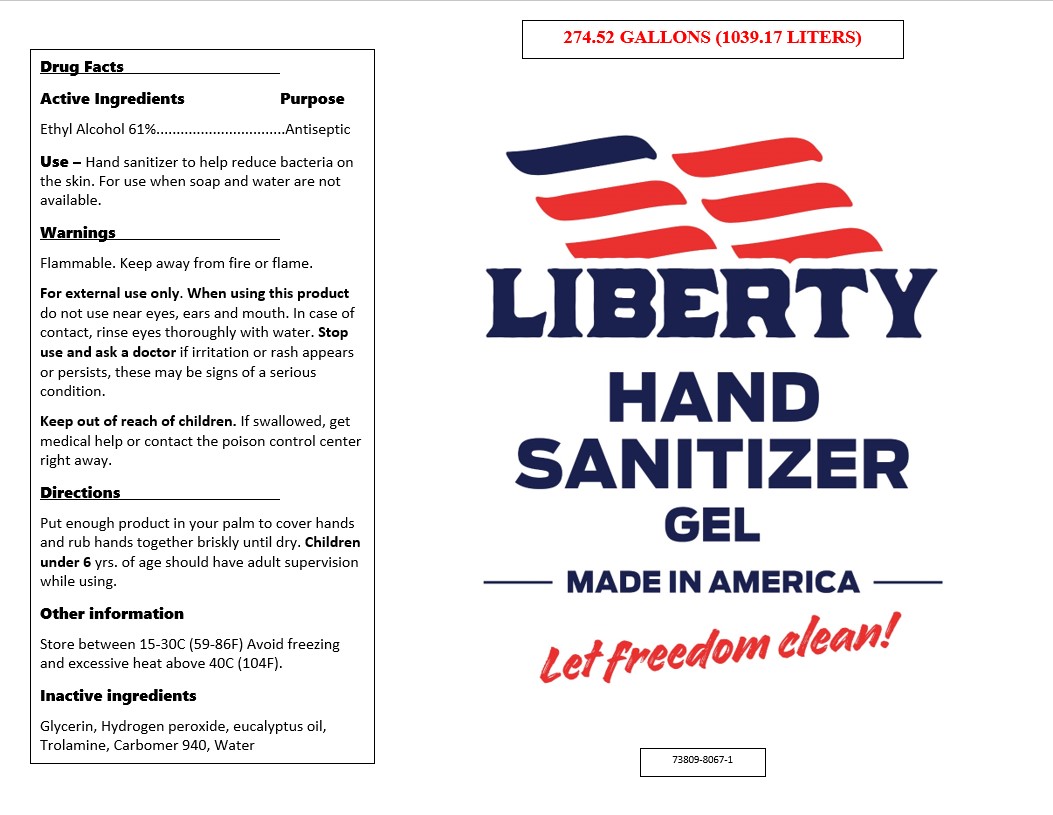 DRUG LABEL: Liberty Hand Sanitizer Gel
NDC: 73809-8067 | Form: GEL
Manufacturer: Surry Chemicals, Inc.
Category: otc | Type: HUMAN OTC DRUG LABEL
Date: 20201229

ACTIVE INGREDIENTS: ALCOHOL 61 L/100 L
INACTIVE INGREDIENTS: EUCALYPTUS OIL 0.0007 L/100 L; CARBOMER 940 0.229 L/100 L; GLYCERIN 1.45 L/100 L; HYDROGEN PEROXIDE 0.095 L/100 L; WATER; TROLAMINE 0.0046 L/100 L

Active Ingredient(s)

Alcohol 61% v/v. Purpose: Antiseptic

Purpose

Antiseptic, Hand Sanitizer

Use

Hand Sanitizer to help reduce bacteria that potentially can cause disease. For use when soap and water are not available.

Warnings

For external use only. Flammable. Keep away from heat or flame

Do not use

- in children less than 2 months of age
- on open skin wounds

When using this product keep out of eyes, ears, and mouth. In case of contact with eyes, rinse eyes thoroughly with water.
Stop use and ask a doctor if irritation or rash occurs. These may be signs of a serious condition.
Keep out of reach of children. If swallowed, get medical help or contact a Poison Control Center right away.

Stop use and ask a doctor if irritation or rash occurs. These may be signs of a serious condition.

Keep out of reach of children. If swallowed, get medical help or contact a Poison Control Center right away.

Directions

- Place enough product on hands to cover all surfaces. Rub hands together until dry.
- Supervise children under 6 years of age when using this product to avoid swallowing.

Other information

- Store between 15-30C (59-86F)
- Avoid freezing and excessive heat above 40C (104F)

Inactive ingredients

glycerin, hydrogen peroxide, trolamine, eucalyptus oil, purified water USP

Package Label - Principal Display Panel

1048L NDC: 73809-8067-1

208 L NDC: 73809-8067-2

18.9 L NDC: 73809-8067-3

3.785 L NDC: 73809-8067-4

1.893L NDC: 73809-8067-5

1.893 L NDC: 73809-8067-5